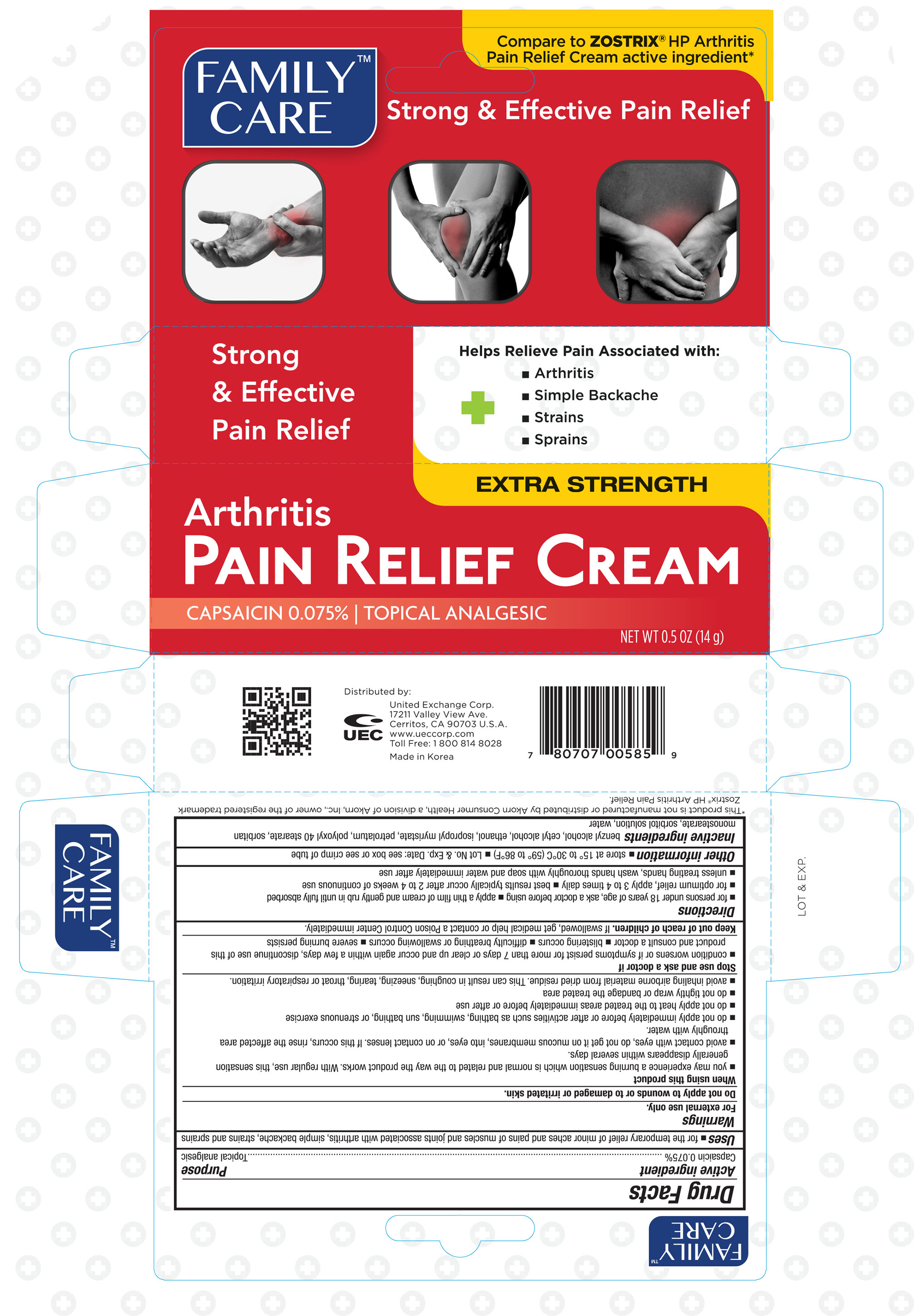 DRUG LABEL: Family Care Arthritis Pain Relief
NDC: 65923-585 | Form: CREAM
Manufacturer: United Excahnge Corp.
Category: otc | Type: HUMAN OTC DRUG LABEL
Date: 20160726

ACTIVE INGREDIENTS: CAPSAICIN 0.75 mg/1 g
INACTIVE INGREDIENTS: BENZYL ALCOHOL; CETYL ALCOHOL; ALCOHOL; ISOPROPYL MYRISTATE; PETROLATUM; POLYOXYL 40 STEARATE; SORBITAN MONOSTEARATE; SORBITOL; WATER

Active ingredient Purpose

Capsaicin 0.075%............................................................ Topical analgesic

Uses

- for the temporary relief of minor aches and pains of muscles and joints associated with arthritis, simple backache, strains, and sprains

Warnings

For external use only.

Do not apply to wounds or to damaged or irritated skin.

When using this product

- you may experience a burning sensation which is normal and related to the way the product works. With regular use, this sensation generally disapperas within several days.
- avoid contact with eyes, do not get on mucous membranes, into eyes, or on contact lesnes. If this occurs, rinse the affected area throughly with water.
- do not apply immediately before or after activities such as bathing, swimming, sun bathing, or strenuous excercise
- do not apply heat to the treated areas immediately before or after use
- do not tightly wrap or bandage the treated area
- avoid inhaling airborne material from dried residue. This can result in coughing, sneezing, tearing, throat or respiratory irritation.

Stop use and ask a doctor if

- condition worsens or if symptoms persist for more than 7 days or clear up and occur again within a few days, discontinue use of this product and consult a doctor
- blistering occurs
- difficulty breathing or swallowing occurs
- severe burning persists

Keep out of reach of children. If swallowed, get medical help or contact a Poison Control Center immediately.

Directions

- for persons under 18 years of age, ask a doctor before using
- apply a thin film of cream and gently rub in until fully absorbed
- for optimum relief, apply 3 to 4 times daily
- best results typically occur after 2 to 4 weeks of continuous use
- unless treating hands, wash hands throughly with soap and water immediately after use

Other information

- store at 15° to 30°C (59° to 86°F)
- Lot No. & Exp. Date: see box or see crimp of tube

Inactive ingredients

benzyl alcohol, cetyl alcohol, ethanol, isopropyl myristate, petrolatum, polyoxyl 40 stearate, sobritan monostearate, sorbitol solution, water

DOSAGE AND ADMINISTRATION

Distributed by:

United Exchange Corp.

17211 Valley View Ave.

Cerritos, CA 90703 U.S.A.

www.ueccorp.com

Toll Free: 1 800 814 8028

Made in Korea